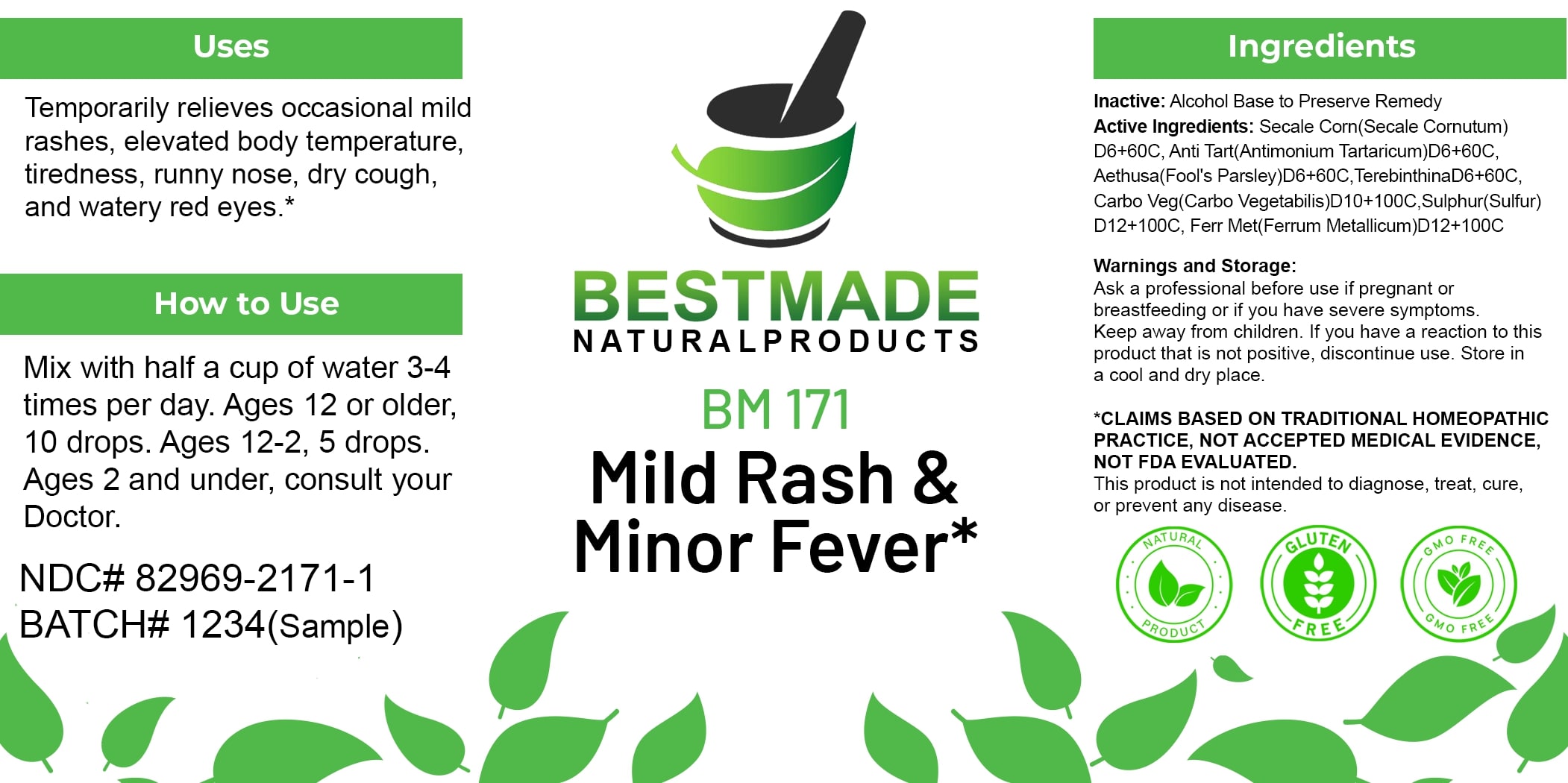 DRUG LABEL: Bestmade Natural Products BM171
NDC: 82969-2171 | Form: LIQUID
Manufacturer: Bestmade Natural Products
Category: homeopathic | Type: HUMAN OTC DRUG LABEL
Date: 20250219

ACTIVE INGREDIENTS: ACTIVATED CHARCOAL 30 [hp_C]/30 [hp_C]; ANTIMONY POTASSIUM TARTRATE 30 [hp_C]/30 [hp_C]; TURPENTINE OIL 30 [hp_C]/30 [hp_C]; CLAVICEPS PURPUREA SCLEROTIUM 30 [hp_C]/30 [hp_C]; IRON 30 [hp_C]/30 [hp_C]; AETHUSA CYNAPIUM 30 [hp_C]/30 [hp_C]; SULFUR 30 [hp_C]/30 [hp_C]
INACTIVE INGREDIENTS: ALCOHOL 30 [hp_C]/30 [hp_C]

BM171

DOSAGE AND ADMINISTRATION

How to Use

Mix with half a cup of water 3-4 times per day. Ages 12 or older, 10 drops. Ages 12-2, 5 drops. Ages 2 and under, consult your Doctor.

INACTIVE INGREDIENT

Ingredients

Inactive: Alcohol Base to Preserve Remedy

ACTIVE INGREDIENT

Active Ingredients: Secale Corn(Secale Comutum) D6+60C, Ant Tart(Antimonium Tartaricum)D6+60C, Aethusa(Fool's Parsley)D6+60C, TerebinthinaD6+60C, Carbo Veg(Carbo Vegetabilis)D10+100C, Sulphur(Sulfur) D12+100C, Ferr Met(Ferrum Metallicum)D12+100C

Uses

Temporarily relieves occasional mild rashes, elevated body temperature, tiredness, runny nose, dry cough, and watery red eyes.*

*CLAIMS BASED ON TRADITIONAL HOMEOPATHIC PRACTICE, NOT ACCEPTED MEDICAL EVIDENCE. NOT FDA EVALUATED.

This product is not intended to diagnose, treat, cure, or prevent any disease.

Uses

Temporarily relieves occasional mild rashes, elevated body temperature, tiredness, runny nose, dry cough, and watery red eyes.*

*CLAIMS BASED ON TRADITIONAL HOMEOPATHIC PRACTICE, NOT ACCEPTED MEDICAL EVIDENCE. NOT FDA EVALUATED.

This product is not intended to diagnose, treat, cure, or prevent any disease.

KEEP OUT OF REACH OF CHILDREN

Warnings and Storage:

Ask a professional before use if pregnant or breastfeeding or if you have severe symptoms. Keep away from children. If you have a reaction to this product that is not positive, discontinue use. Store in a cool and dry place.

Warnings and Storage:

Ask a professional before use if pregnant or breastfeeding or if you have severe symptoms. Keep away from children. If you have a reaction to this product that is not positive, discontinue use. Store in a cool and dry place.

*CLAIMS BASED ON TRADITIONAL HOMEOPATHIC PRACTICE, NOT ACCEPTED MEDICAL EVIDENCE. NOT FDA EVALUATED.

This product is not intended to diagnose, treat, cure, or prevent any disease.

Entire package label